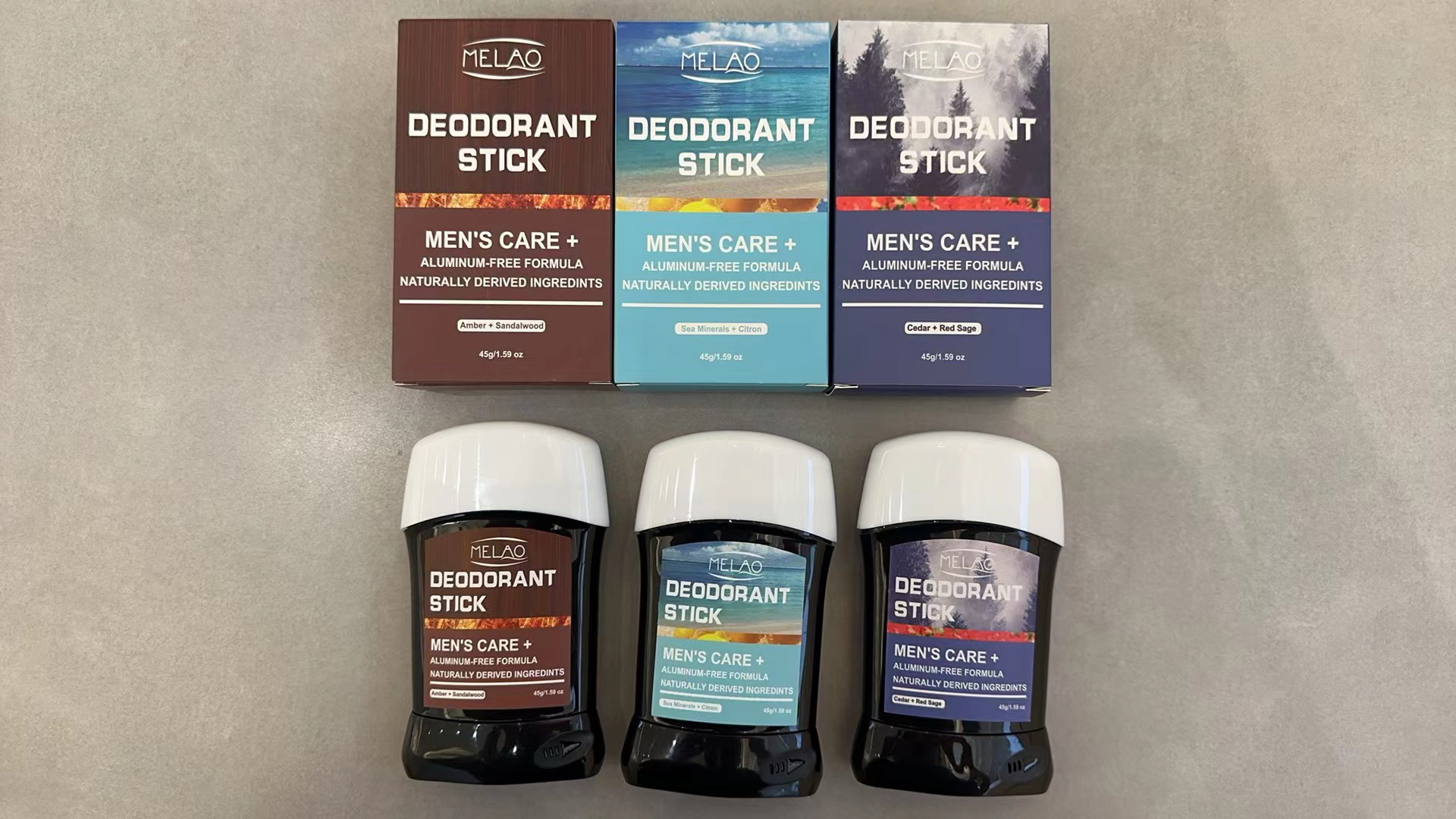 DRUG LABEL: MELAO Deodorant Stick
NDC: 83566-996 | Form: STICK
Manufacturer: Guangzhou Yilong Cosmetics Co., Ltd
Category: otc | Type: HUMAN OTC DRUG LABEL
Date: 20240806

ACTIVE INGREDIENTS: .ALPHA.-BISABOLOL, (+)- 1 g/100 g
INACTIVE INGREDIENTS: COCONUT OIL; BUTYLATED HYDROXYTOLUENE; GLYCERYL STEARATE/PEG-75 STEARATE; PROPYLPARABEN; ETHYLHEXYL PALMITATE; PARAFFIN; PEG-8 BEESWAX; PEG-60 SORBITAN STEARATE; MAGNESIUM HYDROXIDE; TOCOPHEROL

MELAO Deodorant Stick

ACTIVE INGREDIENT

Bisabolol 1%

INACTIVE INGREDIENT

Cyclopentasiloxane 57%

Magnesium Hydroxide 7%

Beeswax 7%

Ethylhexyl Palmitate 5%

Ozokerite 4%

Paraffin 4%

Cocos Nucifera(Coconut) Oil 3.70%

Glyceryl Stearate 3.60%

Sorbitan Stearate 2.40%

Aroma 2.30%

Tocopherol 2%

BHT 0.90%

Propylparaben 0.1%

PURPOSE

Correcting body odor

INDICATIONS AND USAGE

STEP1: Clean and thoroughly dry your skin.
STEP2: Twist the bottom of the product.
STEP3: Gently apply to the underarms or other desired areas.

WARNINGS

1. For external use only.

Stop use and ask a doctor if rash occurs.

Do not use on damaged or broken skin.

When using this product keep out of eyes. Rinse with water to remove.

DOSAGE AND ADMINISTRATION

STEP1: Clean and thoroughly dry your skin.
STEP2: Twist the bottom of the product.
STEP3: Gently apply to the underarms or other desired areas.

Keep out of reach of children. If swallowed, get medical help or contact a Poison Control Center right away.